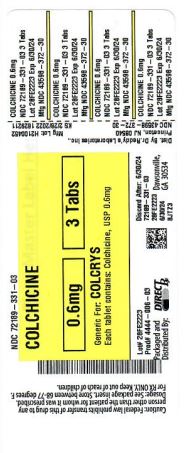 DRUG LABEL: COLCHICINE
NDC: 72189-331 | Form: TABLET
Manufacturer: Direct Rx
Category: prescription | Type: HUMAN PRESCRIPTION DRUG LABEL
Date: 20250121

ACTIVE INGREDIENTS: COLCHICINE 0.6 mg/1 1
INACTIVE INGREDIENTS: TRIACETIN; FD&C BLUE NO. 2; POLYDEXTROSE; STARCH, CORN; SODIUM STARCH GLYCOLATE TYPE A CORN; LACTOSE MONOHYDRATE; FD&C RED NO. 40; HYPROMELLOSE 2208 (100 MPA.S); POLYETHYLENE GLYCOL, UNSPECIFIED; CELLULOSE, MICROCRYSTALLINE; TITANIUM DIOXIDE; MAGNESIUM STEARATE

Colchicine

INDICATIONS AND USAGE

1.1 Gout Flares

Colchicine tablets are indicated for prophylaxis and the treatment of acute gout flares.

•
Prophylaxis of Gout Flares: Colchicine tablets are indicated for prophylaxis of gout flares.
•
Treatment of Gout Flares: Colchicine tablets are indicated for treatment of acute gout flares when taken at the first sign of a flare.

1.2 Familial Mediterranean Fever (FMF)

Colchicine tablets are indicated in adults and children four years or older for treatment of familial Mediterranean fever (FMF).

DOSAGE AND ADMINISTRATION

The long-term use of colchicine is established for FMF and the prophylaxis of gout flares, but the safety and efficacy of repeat treatment for gout flares has not been evaluated. The dosing regimens for colchicine tablets are different for each indication and must be individualized.

The recommended dosage of colchicine tablets depends on the patient’s age, renal function, hepatic function and use of coadministered drugs [see DOSAGE AND ADMINISTRATION (2.4, 2.5, 2.6)].

Colchicine tablets are administered orally without regard to meals.

Colchicine tablets are not an analgesic medication and should not be used to treat pain from other causes.

2.1 Gout Flares

Prophylaxis of Gout Flares

The recommended dosage of colchicine tablets for prophylaxis of gout flares for adults and adolescents older than 16 years of age is 0.6 mg once or twice daily. The maximum recommended dose for prophylaxis of gout flares is 1.2 mg/day.

An increase in gout flares may occur after initiation of uric acid-lowering therapy, including pegloticase, febuxostat and allopurinol, due to changing serum uric acid levels resulting in mobilization of urate from tissue deposits. Colchicine tablets are recommended upon initiation of gout flare prophylaxis with uric acid-lowering therapy. Prophylactic therapy may be beneficial for at least the first six months of uric acid-lowering therapy.

Treatment of Gout Flares

The recommended dose of colchicine tablets for treatment of a gout flare is 1.2 mg (two tablets) at the first sign of the flare followed by 0.6 mg (one tablet) one hour later. Higher doses have not been found to be more effective. The maximum recommended dose for treatment of gout flares is 1.8 mg over a 1-hour period. Colchicine tablets may be administered for treatment of a gout flare during prophylaxis at doses not to exceed 1.2 mg (two tablets) at the first sign of the flare followed by 0.6 mg (one tablet) one hour later. Wait 12 hours and then resume the prophylactic dose.

2.2 FMF

The recommended dosage of colchicine tablets for FMF in adults is 1.2 mg to 2.4 mg daily.

Colchicine tablets should be increased as needed to control disease and as tolerated in increments of 0.3 mg/day to a maximum recommended daily dose. If intolerable side effects develop, the dose should be decreased in increments of 0.3 mg/day. The total daily colchicine tablets dose may be administered in one to two divided doses.

2.3 Recommended Pediatric Dosage

Prophylaxis and Treatment of Gout Flares

Colchicine tablets are not recommended for pediatric use in prophylaxis or treatment of gout flares.

FMF

The recommended dosage of colchicine tablets for FMF in pediatric patients 4 years of age and older is based on age. The following daily doses may be given as a single or divided dose twice daily:

•
Children 4 to 6 years: 0.3 mg to 1.8 mg daily
•
Children 6 to 12 years: 0.9 mg to 1.8 mg daily
•
Adolescents older than 12 years: 1.2 mg to 2.4 mg daily

2.4 Dose Modification for Coadministration of Interacting Drugs

Concomitant Therapy

Coadministration of colchicine tablets with drugs known to inhibit CYP3A4 and/or P-glycoprotein (P-gp) increases the risk of colchicine-induced toxic effects (Table 1). If patients are taking or have recently completed treatment with drugs listed in Table 1 within the prior 14 days, the dose adjustments are as shown in the table below [see DRUG INTERACTIONS (7)].

Table 1. Colchicine Tablets Dose Adjustment for Coadministration with Interacting Drugs if No Alternative Available*

*
For magnitude of effect on colchicine plasma concentrations [see CLINICAL PHARMACOLOGY (12.3)]
†
Patients with renal or hepatic impairment should not be given colchicine tablets in conjunction with strong CYP3A4 or P-gp inhibitors [see CONTRAINDICATIONS (4)]
‡
When used in combination with Ritonavir, see dosing recommendations for strong CYP3A4 inhibitors [see CONTRAINDICATIONS (4)]

Strong CYP3A4 Inhibitors†

Gout Flares

Noted or Anticipated Outcome

Prophylaxis of Gout Flares

Treatment of Gout Flares

FMF

Drug

Original Intended Dosage

Adjusted Dose

Original Intended Dosage

Adjusted Dose

Original Intended Dosage

Adjusted Dose

Atazanavir

Clarithromycin

Darunavir/

Ritonavir‡

Indinavir

Itraconazole

Ketoconazole

Lopinavir/

Ritonavir

Nefazodone

Nelfinavir

Ritonavir

Saquinavir

Telithromycin

Tipranavir/

Ritonavir

Significant increase in colchicine plasma levels; fatal colchicine toxicity has been reported with clarithromycin, a strong CYP3A4 inhibitor. Similarly, significant increase in colchicine plasma levels is anticipated with other strong CYP3A4 inhibitors

0.6 mg twice a day

0.6 mg once a day

0.3 mg once a day

0.3 mg once every other day

1.2 mg

(2 tablets) followed by 0.6 mg (1 tablet) 1 hour later. Dose to be repeated no earlier than 3 days.

0.6 mg

(1 tablet) x 1 dose, followed by 0.3 mg (1/2 tablet) 1 hour later. Dose to be repeated no earlier than 3 days.

Maximum daily dose of 1.2 mg - 2.4 mg

Maximum daily dose of 0.6 mg (may be given as 0.3 mg twice a day)

Moderate CYP3A4 Inhibitors

Gout Flares

Note or Anticipated Outcome

Prophylaxis of Gout Flares

Treatment of Gout Flares

FMF

Drug

Original Intended Dosage

Adjusted Dosage

Original Intended Dosage

Adjusted Dosage

Original Intended Dosage

Adjusted Dosage

Amprenavir

Aprepitant

Diltiazem

Erythromycin

Fluconazole

Fosamprenavir (prodrug of Amprenavir)

Grapefruit juice

Verapamil

Significant increase in colchicine plasma concentration is anticipated. Neuromuscular toxicity has been reported with diltiazem and verapamil interactions.

0.6 mg twice a day

0.6 mg once a day

0.3 mg twice a day or 0.6 mg once a day

0.3 mg once a day

1.2 mg

(2 tablets) followed by 0.6 mg (1 tablet)

1 hour later. Dose to be repeated no earlier than 3 days.

1.2 mg

(2 tablets) x 1 dose. Dose to be repeated no earlier than 3 days.

Maximum daily dose of 1.2 mg - 2.4 mg

Maximum daily dose of 1.2 mg (may be given as 0.6 mg twice a day)

P-gp Inhibitors

Gout Flares

Note or Anticipated Outcome

Prophylaxis of Gout Flares

Treatment of Gout Flares

FMF

Drug

Original Intended Dosage

Adjusted Dosage

Original Intended Dosage

Adjusted Dosage

Original Intended Dosage

Adjusted Dosage

Cyclosporine

Ranolazine

Significant increase in colchicine plasma levels; fatal colchicine toxicity has been reported with cyclosporine, a P-gp inhibitor. Similarly, significant increase in colchicine plasma levels is anticipated with other

P-gp inhibitors.

0.6 mg twice a day

0.6 mg once a day

0.3 mg once a day

0.3 mg once every other day

1.2 mg

(2 tablets) followed by 0.6 mg

(1 tablet)

1 hour later. Dose to be repeated no earlier than 3 days.

0.6 mg

(1 tablet) x

1 dose. Dose to be repeated no earlier than 3 days.

Maximum daily dose of 1.2 mg - 2.4 mg

Maximum daily dose of 0.6 mg (may be given as 0.3 mg twice a day)

Table 2. Colchicine Tablets Dose Adjustment for Coadministration with Protease Inhibitors

Protease Inhibitor

Clinical Comment

w/ Colchicine - Prophylaxis of Gout Flares

w/o Colchicine – Treatment of Gout Flares

w/Colchicine – Treatment of FMF

Atazanavir

sulfate

(Reyataz)

Patients with renal or hepatic impairment should not be given colchicine with Reyataz.

Original

dose

Adjusted

dose

0.6 mg (1 tablet) x 1 dose, followed by 0.3 mg (1/2 tablet) 1 hour later. Dose to be repeated no earlier than 3 days.

Maximum daily dose of 0.6 mg (may be given as 0.3 mg twice a day)

0.6 mg twice a day

0.6 mg once a day

0.3 mg once a day

0.3 mg once every other day

Darunavir (Prezista)

Patients with renal or hepatic impairment should not be given colchicine with Prezista/ritonavir.

Original dose

Adjusted dose

0.6 mg (1 tablet) x 1 dose, followed by 0.3 mg (1/2 tablet) 1 hour later. Dose to be repeated no earlier than 3 days.

Maximum daily dose of 0.6 mg (may be given as 0.3 mg twice a day)

0.6 mg twice a day

0.6 mg once a day

0.3 mg once a day

0.3 mg once every other day

Fosamprenavir (Lexiva) with Ritonavir

Patients with renal or hepatic impairment should not be given colchicine with Lexiva/ritonavir.

Original dose

Adjusted dose

0.6 mg (1 tablet) x 1 dose, followed by 0.3 mg (1/2 tablet) 1 hour later. Dose to be repeated no earlier than 3 days.

Maximum daily dose of 0.6 mg (may be given as 0.3 mg twice a day)

0.6 mg twice a day

0.6 mg once a day

0.3 mg once a day

0.3 mg once every other day

Fosamprenavir (Lexiva)

Patients with renal or hepatic impairment should not be given colchicine with Lexiva/ritonavir

Original dose

Adjusted dose

1.2 mg (2 tablets) x 1 dose. Dose to be repeated no earlier than 3 days.

Maximum daily dose of 1.2 mg (may be given as 0.6 mg twice a day)

0.6 mg twice a day

0.6 mg once a day

0.3 mg twice a day or 0.6 mg once a day

0.3 mg once a day

Indinavir (Crixivan)

Patients with renal or hepatic impairment should not be given colchicine with Crixivan.

Original dose

Adjusted dose

0.6 mg (1 tablet) x 1 dose, followed by 0.3 mg (1/2 tablet) 1 hour later. Dose to be repeated no earlier than 3 days.

Maximum daily dose of 0.6 mg (may be given as 0.3 mg twice a day)

0.6 mg twice a day

0.6 mg once a day

0.3 mg once a day

0.3 mg once every other day

Lopinavir/

Ritonavir

(Kaletra)

Patients with renal or hepatic impairment should not be given colchicine with Kaletra.

Original dose

Adjusted dose

0.6 mg (1 tablet) x 1 dose, followed by 0.3 mg (1/2 tablet) 1 hour later. Dose to be repeated no earlier than 3 days.

Maximum daily dose of 0.6 mg (may be given as 0.3 mg twice a day)

0.6 mg twice a day

0.6 mg once a day

0.3 mg once a day

0.3 mg once every other day

Nelfinavir mesylate (Viracept)

Patients with renal or hepatic impairment should not be given colchicine with Viracept.

Original dose

Adjusted dose

0.6 mg (1 tablet) x 1 dose, followed by 0.3 mg (1/2 tablet) 1 hour later. Dose to be repeated no earlier than 3 days.

Maximum daily dose of 0.6 mg (may be given as 0.3 mg twice a day)

0.6 mg twice a day

0.6 mg once a day

0.3 mg once a day

0.3 mg once every other day

Ritonavir (Norvir)

Patients with renal or hepatic impairment should not be given colchicine with Norvir.

Original dose

Adjusted dose

0.6 mg (1 tablet) x 1 dose, followed by 0.3 mg (1/2 tablet) 1 hour later. Dose to be repeated no earlier than 3 days.

Maximum daily dose of 0.6 mg (may be given as 0.3 mg twice a day)

0.6 mg twice a day

0.6 mg once a day

0.3 mg once a day

0.3 mg once every other day

Saquinavir mesylate (Invirase)

Patients with renal or hepatic impairment should not be given colchicine with Invirase/ritonavir.

Original dose

Adjusted dose

0.6 mg (1 tablet) x 1 dose, followed by 0.3 mg (1/2 tablet) 1 hour later. Dose to be repeated no earlier than 3 days.

Maximum daily dose of 0.6 mg (may be given as 0.3 mg twice a day)

0.6 mg twice a day

0.6 mg once a day

0.3 mg once a day

0.3 mg once every other day

Tipranavir (Aptivus)

Patients with renal or hepatic impairment should not be given colchicine with Aptivus/ritonavir.

Original dose

Adjusted dose

0.6 mg (1 tablet) x 1 dose, followed by 0.3 mg (1/2 tablet) 1 hour later. Dose to be repeated no earlier than 3 days.

Maximum daily dose of 0.6 mg (may be given as 0.3 mg twice a day)

0.6 mg twice a day

0.6 mg once a day

0.3 mg once a day

0.3 mg once every other day

Treatment of gout flares with colchicine tablets is not recommended in patients receiving prophylactic dose of colchicine tablets and CYP3A4 inhibitors.

2.5 Dose Modification in Renal Impairment

Colchicine dosing must be individualized according to the patient's renal function [see USE IN SPECIFIC POPULATIONS (8.6)].

Clcr in mL/minute may be estimated from serum creatinine (mg/dL) determination using the following formula:

[Dosing Calculation]

Gout Flares

Prophylaxis of Gout Flares

For prophylaxis of gout flares in patients with mild (estimated creatinine clearance [Clcr] 50 to 80 mL/min) to moderate (Clcr 30 to 50 mL/min) renal function impairment, adjustment of the recommended dose is not required, but patients should be monitored closely for adverse effects of colchicine. However, in patients with severe impairment, the starting dose should be 0.3 mg/day and any increase in dose should be done with close monitoring. For the prophylaxis of gout flares in patients undergoing dialysis, the starting doses should be 0.3 mg given twice a week with close monitoring [see CLINICAL PHARMACOLOGY (12.3), USE IN SPECIFIC POPULATIONS (8.6)].

Treatment of Gout Flares

For treatment of gout flares in patients with mild (Clcr 50 to 80 mL/min) to moderate (Clcr 30 to 50 mL/min) renal function impairment, adjustment of the recommended dose is not required, but patients should be monitored closely for adverse effects of colchicine. However, in patients with severe impairment, while the dose does not need to be adjusted for the treatment of gout flares, a treatment course should be repeated no more than once every two weeks. For patients with gout flares requiring repeated courses, consideration should be given to alternate therapy. For patients undergoing dialysis, the total recommended dose for the treatment of gout flares should be reduced to a single dose of 0.6 mg (one tablet). For these patients, the treatment course should not be repeated more than once every two weeks [see CLINICAL PHARMACOLOGY (12.3), USE IN SPECIFIC POPULATIONS (8.6)].

Treatment of gout flares with colchicine tablets is not recommended in patients with renal impairment who are receiving colchicine tablets for prophylaxis.

FMF

Caution should be taken in dosing patients with moderate and severe renal impairment and in patients undergoing dialysis. For these patients, the dosage should be reduced [see CLINICAL PHARMACOLOGY (12.3)]. Patients with mild (Clcr 50 to 80 mL/min) and moderate (Clcr 30 to 50 mL/min) renal impairment should be monitored closely for adverse effects of colchicine tablets. Dose reduction may be necessary. For patients with severe renal failure (Clcr less than 30 mL/min), start with 0.3 mg/day; any increase in dose should be done with adequate monitoring of the patient for adverse effects of colchicine [see USE IN SPECIFIC POPULATIONS (8.6)]. For patients undergoing dialysis, the total recommended starting dose should be 0.3 mg (half tablet) per day. Dosing can be increased with close monitoring. Any increase in dose should be done with adequate monitoring of the patient for adverse effects of colchicine [see CLINICAL PHARMACOLOGY (12.3), USE IN SPECIFIC POPULATIONS (8.6)].

2.6 Dose Modification in Hepatic Impairment

Gout Flares

Prophylaxis of Gout Flares

For prophylaxis of gout flares in patients with mild to moderate hepatic function impairment, adjustment of the recommended dose is not required, but patients should be monitored closely for adverse effects of colchicine. Dose reduction should be considered for the prophylaxis of gout flares in patients with severe hepatic impairment [see USE IN SPECIFIC POPULATIONS (8.7)].

Treatment of Gout Flares

For treatment of gout flares in patients with mild to moderate hepatic function impairment, adjustment of the recommended dose is not required, but patients should be monitored closely for adverse effects of colchicine. However, for the treatment of gout flares in patients with severe impairment, while the dose does not need to be adjusted, a treatment course should be repeated no more than once every two weeks. For these patients, requiring repeated courses for the treatment of gout flares, consideration should be given to alternate therapy [see USE IN SPECIFIC POPULATIONS (8.7)].

Treatment of gout flares with colchicine tablets is not recommended in patients with hepatic impairment who are receiving colchicine tablets for prophylaxis.

FMF

Patients with mild to moderate hepatic impairment should be monitored closely for adverse effects of colchicine. Dose reduction should be considered in patients with severe hepatic impairment [see USE IN SPECIFIC POPULATIONS (8.7)].

CLOSE

DOSAGE FORMS AND STRENGTHS

Colchicine Tablets USP, 0.6 mg — purple color, film-coated, capsule shaped tablets debossed with ‘ [logo] 372’ on one side and score line on the other side of the tablet.

CONTRAINDICATIONS

Patients with renal or hepatic impairment should not be given colchicine tablets in conjunction with P-gp or strong CYP3A4 inhibitors (this includes all protease inhibitors except fosamprenavir). In these patients, life-threatening and fatal colchicine toxicity has been reported with colchicine taken in therapeutic doses.

16.1 How Supplied

Colchicine Tablets USP, 0.6 mg are purple colored, film-coated, capsule shaped tablets debossed with ‘Stylized Y 372’ on one side and score line on the other side of the tablet.

Bottles of 30 NDC 43598-372-30

Bottles of 100 NDC 43598-372-01

Bottles of 1,000 NDC 43598-372-10

16.2 Storage

Store at 20° to 25°C (68° to 77°F) [See USP Controlled Room Temperature].

Protect from light.

DISPENSE IN TIGHT, LIGHT-RESISTANT CONTAINER.

PATIENT COUNSELING INFORMATION

Advise the patient to read the FDA-approved patient labeling (MEDICATION GUIDE).

Dosing Instructions: Patients should be advised to take colchicine tablets as prescribed, even if they are feeling better. Patients should not alter the dose or discontinue treatment without consulting with their doctor. If a dose of colchicine tablets is missed:

•
For treatment of a gout flare when the patient is not being dosed for prophylaxis, take the missed dose as soon as possible.
•
For treatment of a gout flare during prophylaxis, take the missed dose immediately, wait 12 hours, then resume the previous dosing schedule.
•
For prophylaxis without treatment for a gout flare, or FMF, take the dose as soon as possible and then return to the normal dosing schedule. However, if a dose is skipped the patient should not double the next dose.

Fatal Overdose: Instruct patient that fatal overdoses, both accidental and intentional, have been reported in adults and children who have ingested colchicine. Colchicine tablets should be kept out of the reach of children.

Blood Dyscrasias: Patients should be informed that bone marrow depression with agranulocytosis, aplastic anemia and thrombocytopenia may occur with colchicine tablets.

Drug and Food Interactions: Patients should be advised that many drugs or other substances may interact with colchicine tablets and some interactions could be fatal. Therefore, patients should report to their healthcare provider all of the current medications they are taking and check with their healthcare provider before starting any new medications, particularly antibiotics. Patients should also be advised to report the use of nonprescription medication or herbal products. Grapefruit and grapefruit juice may also interact and should not be consumed during colchicine tablets treatment.

Neuromuscular Toxicity: Patients should be informed that muscle pain or weakness, tingling or numbness in fingers or toes may occur with colchicine tablets alone or when it is used with certain other drugs. Patients developing any of these signs or symptoms must discontinue colchicine tablets and seek medical evaluation immediately.

Infertility: Advise males of reproductive potential that colchicine tablets may rarely and transiently impair fertility [see USE IN SPECIFIC POPULATIONS (8.3)].

CLOSE

MEDICATION GUIDE

Colchicine Tablets, USP

(KOL-chi-seen)

for oral use

Read the Medication Guide that comes with colchicine tablets before you start taking it and each time you get a refill. There may be new information. This Medication Guide does not take the place of talking to your healthcare provider about your medical condition or treatment. You and your healthcare provider should talk about colchicine tablets when you start taking it and at regular checkups.

What is the most important information that I should know about colchicine tablets?

Colchicine tablets can cause serious side effects or death if levels of colchicine are too high in your body.

•
Taking certain medicines with colchicine tablets can cause your level of colchicine to be too high, especially if you have kidney or liver problems.
•
Tell your healthcare provider about all your medical conditions, including if you have kidney or liver problems. Your dose of colchicine tablets may need to be changed.
•
Tell your healthcare provider about all the medicines you take, including prescription and nonprescription medicines, vitamins and herbal supplements.
•
Even medicines that you take for a short period of time, such as antibiotics, can interact with colchicine tablets and cause serious side effects or death.
•
Talk to your healthcare provider or pharmacist before taking any new medicine.
•
Especially tell your healthcare provider if you take:

•
atazanavir sulfate (Reyataz)
•
cyclosporine (Neoral, Gengraf, Sandimmune)
•
fosamprenavir (Lexiva) with ritonavir
•
indinavir (Crixivan)
•
ketoconazole (Nizoral)
•
nefazodone (Serzone)
•
ritonavir (Norvir)
•
telithromycin (Ketek)

•
clarithromycin (Biaxin)
•
darunavir (Prezista)
•
fosamprenavir (Lexiva)
•
itraconazole (Sporanox)
•
lopinavir/ritonavir (Kaletra)
•
nelfinavir mesylate (Viracept)
•
saquinavir mesylate (Invirase)
•
tipranavir (Aptivus)

Ask your healthcare provider or pharmacist if you are not sure if you take any of the medicines listed above. This is not a complete list of all the medicines that can interact with colchicine tablets.

•
Know the medicines you take. Keep a list of them and show it to your healthcare provider and pharmacist when you get a new medicine.
•
Keep colchicine tablets out of the reach of children.

What are colchicine tablets?

Colchicine tablets are a prescription medicine used to:

•
prevent and treat gout flares in adults
•
treat familial Mediterranean fever (FMF) in adults and children age 4 or older

Colchicine tablets are not a pain medicine, and it should not be taken to treat pain related to other conditions unless specifically prescribed for those conditions.

Who should not take colchicine tablets?

Do not take colchicine tablets if you have liver or kidney problems and you take certain other medicines. Serious side effects, including death, have been reported in these patients even when taken as directed. See “What is the most important information that I should know about colchicine tablets?”

What should I tell my healthcare provider before starting colchicine tablets? See “What is the most important information that I should know about colchicine tablets?”

Before you take colchicine tablets, tell your healthcare provider about all your medical conditions, including if you:

•
have liver or kidney problems.
•
are pregnant or plan to become pregnant. It is not known if colchicine tablets will harm your unborn baby. Talk to your healthcare provider if you are pregnant or plan to become pregnant.
•
are a male with a female partner who can become pregnant. Receiving treatment with colchicine tablets may be related to infertility in some men that is reversible when treatment is stopped.
•
are breastfeeding or plan to breastfeed. Colchicine passes into your breast milk. You and your healthcare provider should decide if you will take colchicine tablets while breastfeeding. If you take colchicine tablets and breastfeed, you should talk to your child’s healthcare provider about how to watch for side effects in your child.

Tell your healthcare provider about all the medicines you take, including ones that you may only be taking for a short time, such as antibiotics. See “What is the most important information that I should know about colchicine tablets?”
Do not start a new medicine without talking to your healthcare provider.

Using colchicine tablets with certain other medicines, such as cholesterol-lowering medications and digoxin, can affect each other, causing serious side effects. Your healthcare provider may need to change your dose of colchicine tablets. Talk to your healthcare provider about whether the medications you are taking might interact with colchicine tablets and what side effects to look for.

How should I take colchicine tablets?

•
Take colchicine tablets exactly as your healthcare provider tells you to take it. If you are not sure about your dosing, call your healthcare provider.
•
Colchicine tablets can be taken with or without food.
•
If you take too many colchicine tablets, go to the nearest hospital emergency room right away.
•
Do not stop taking colchicine tablets even if you start to feel better, unless your healthcare provider tells you.
•
Your healthcare provider may do blood tests while you take colchicine tablets.
•
If you take colchicine tablets daily and you miss a dose, then take it as soon as you remember. If it is almost time for your next dose, just skip the missed dose. Take the next dose at your regular time. Do not take 2 doses at the same time.

•
If you have a gout flare while taking colchicine tablets daily, report this to your healthcare provider.

What should I avoid while taking colchicine tablets?

Avoid eating grapefruit or drinking grapefruit juice while taking colchicine tablets. It can increase your chances of getting serious side effects.

What are the possible side effects of colchicine tablets?

Colchicine tablets can cause serious side effects or even cause death. See “What is the most important information that I should know about colchicine tablets?”

Get medical help right away if you have:

•
Muscle weakness or pain
•
Numbness or tingling in your fingers or toes
•
Unusual bleeding or bruising
•
Increased infections
•
Feel weak or tired
•
Pale or gray color to your lips, tongue or palms of your hands
•
Severe diarrhea or vomiting

Gout Flares: The most common side effect of colchicine tablets in people who have gout flares is diarrhea.

FMF: The most common side effects of colchicine tablets in people who have FMF are abdominal pain, diarrhea, nausea and vomiting.

Tell your healthcare provider if you have any side effect that bothers you or that does not go away. These are not all of the possible side effects of colchicine tablets. For more information, ask your healthcare provider or pharmacist.

Call your doctor for medical advice about side effects. You may report side effects to FDA at 1-800-FDA-1088.

How should I store colchicine tablets?

•
Store colchicine tablets at room temperature between 20° to 25°C (68° to 77°F).
•
Keep colchicine tablets in a tightly closed container.
•
Keep colchicine tablets out of the light.

Keep colchicine tablets and all medicines out of the reach of children.

General Information about colchicine tablets

Medicines are sometimes prescribed for purposes other than those listed in a Medication Guide. Do not use colchicine tablets for a condition for which it was not prescribed. Do not give colchicine tablets to other people, even if they have the same symptoms that you have. It may harm them. This Medication Guide summarizes the most important information about colchicine tablets. If you would like more information, talk with your healthcare provider. You can ask your healthcare provider or pharmacist for information about colchicine tablets that is written for healthcare professionals.

What are the ingredients in colchicine tablets?

Active Ingredient: colchicine.

Inactive Ingredients: FD&C BLUE #2, FD&C RED #40, hypromellose, lactose monohydrate, macrogol, magnesium stearate, microcrystalline cellulose, polydextrose, pregelatinized starch, sodium starch glycolate, titanium dioxide and triacetin.
All other trademarks are the property of their respective owners.
For more information, call Dr. Reddy’s Laboratories, Inc. at 1-888-375-3784.

Rx Only
Distributor:
Dr. Reddy’s Laboratories Inc.,
Princeton, NJ 08540
Made in India

This Medication Guide has been approved by the U.S. Food and Drug Administration

Revised: 03/2021